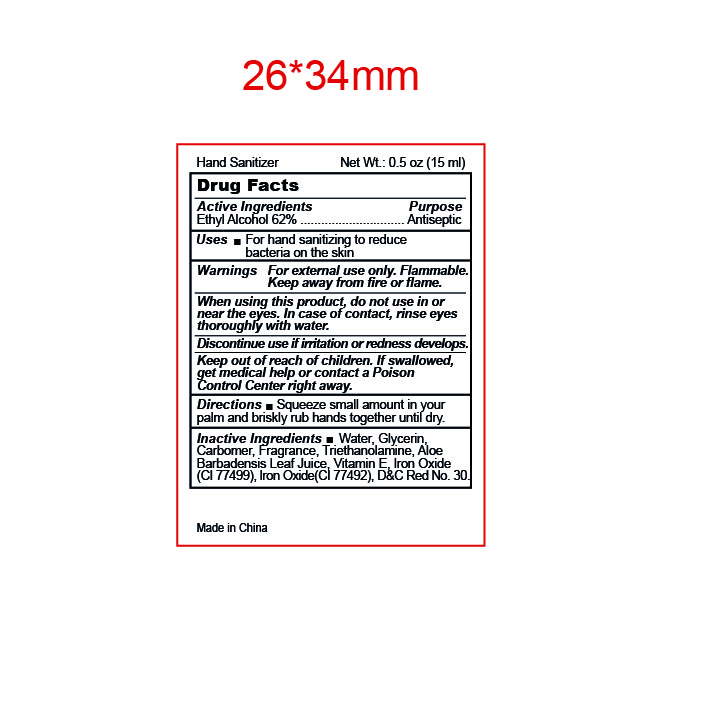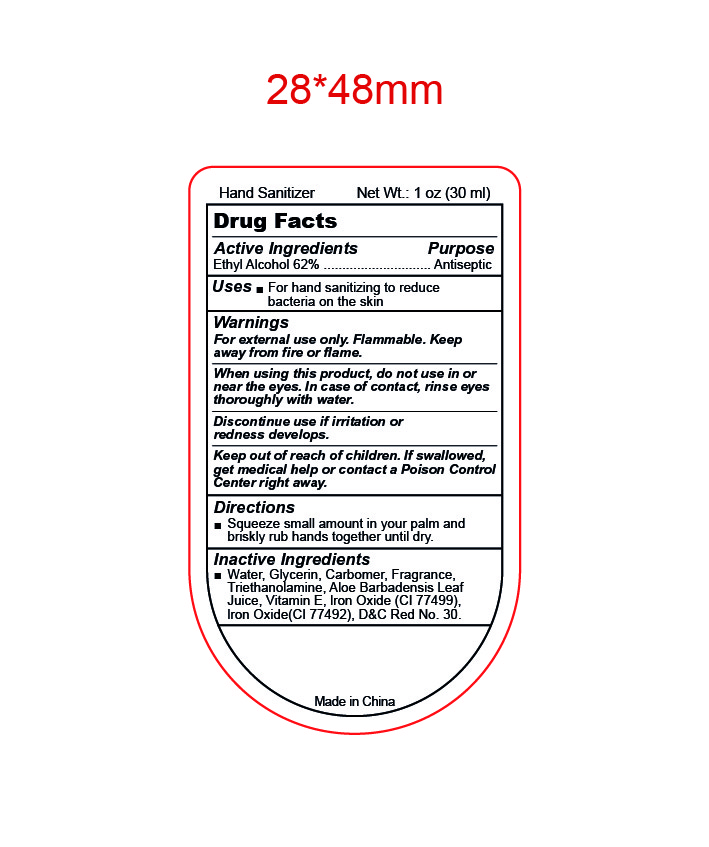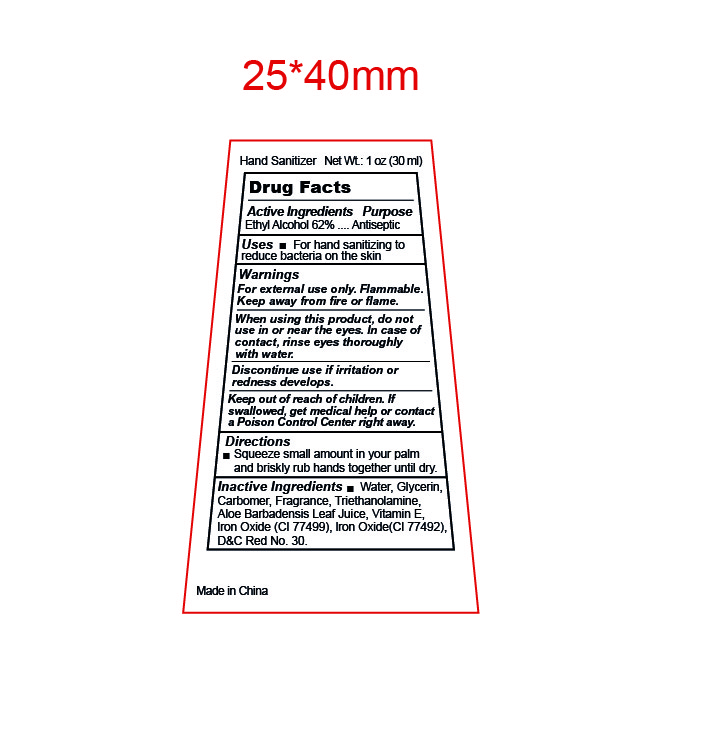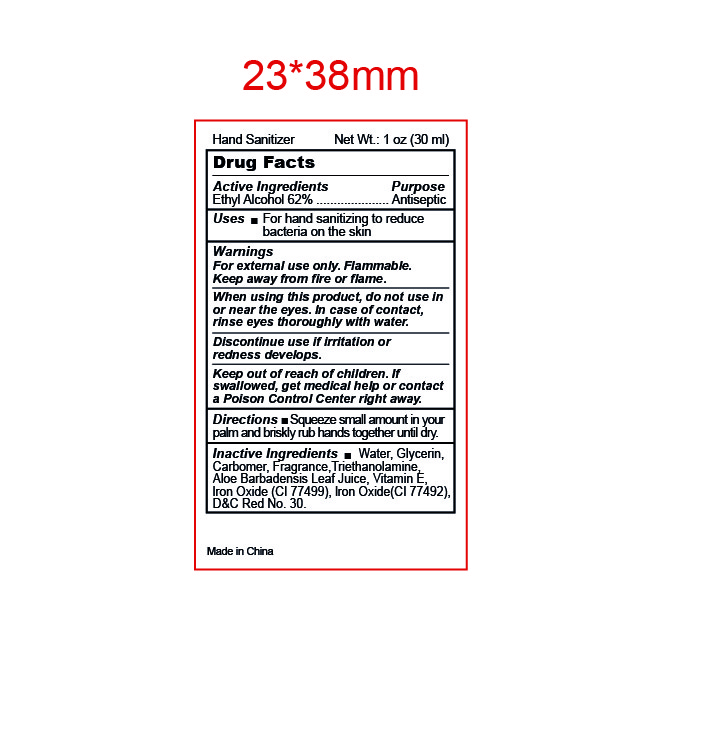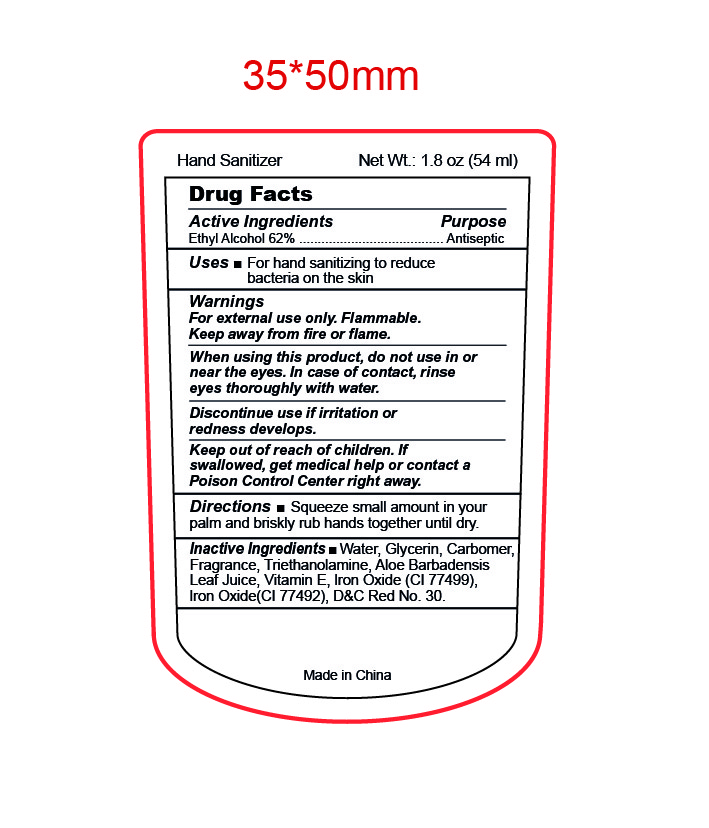 DRUG LABEL: Hand Sanitizer
NDC: 87001-002 | Form: GEL
Manufacturer: HAIAN KANGRUI TEXTILE CO., LTD.
Category: otc | Type: HUMAN OTC DRUG LABEL
Date: 20250812

ACTIVE INGREDIENTS: ALCOHOL 62 g/112 mL
INACTIVE INGREDIENTS: CARBOMER INTERPOLYMER TYPE B (ALLYL PENTAERYTHRITOL CROSSLINKED); .ALPHA.-TOCOPHEROL; FERROSOFERRIC OXIDE; FERRIC OXIDE YELLOW; TROLAMINE; GLYCERIN; WATER; D&C RED NO. 30; ALOE VERA LEAF

87001-002

Active Ingredient

Ethyl Alcohol 62%

Purpose

Antiseptic

Uses

For hand sanitizing to reduce bacteria on the skin.

Warnings

For external use only.

Flammable. Keep away from fire and flame.

When using this product，

do not use in or near the eyes.In case of contact，rinse eyes thoroughly with water.

Discontinue use

if irritation or redness develops.

Keep out of reach of children.

If swallowed, get medical help or contact a Poison Control Center right away.

Directions

Squeeze small amount in your palm and briskly rub hands together until dry.

Inactive ingredients

Water, Glycerin, Carbomer, Fragrance, Triethanolamine, Aloe Barbadensis Leaf Juice, Vitamin E, Iron Oxide(CI 77499), Iron Oxide(CI 77492), D&C RED NO. 30